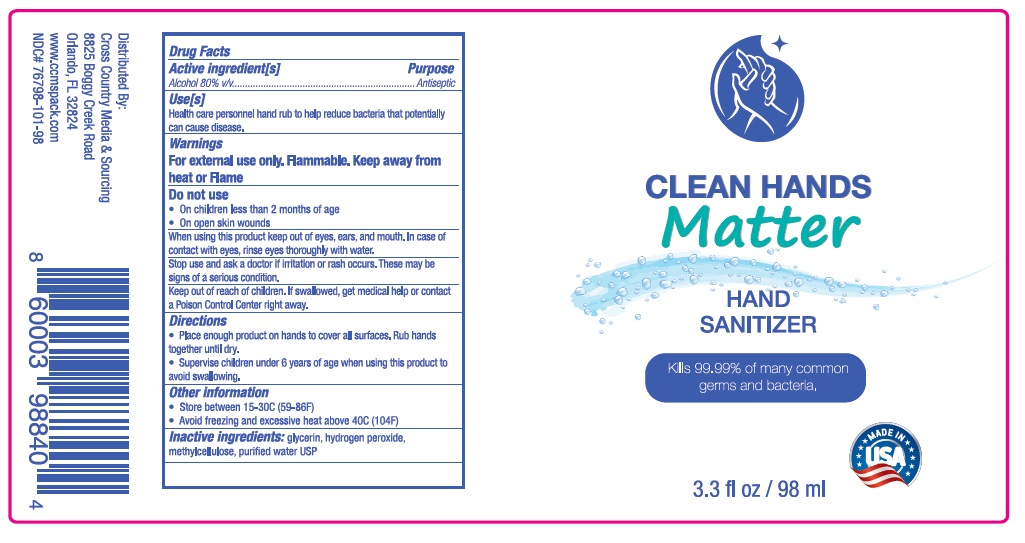 DRUG LABEL: Clean Hands Matter
NDC: 76798-101 | Form: GEL
Manufacturer: Cross Country M & S Inc
Category: otc | Type: HUMAN OTC DRUG LABEL
Date: 20200507

ACTIVE INGREDIENTS: ALCOHOL 80 mL/100 mL
INACTIVE INGREDIENTS: GLYCERIN; HYDROGEN PEROXIDE; METHYLCELLULOSE, UNSPECIFIED; WATER

CLEAN HANDS Matter HAND SANITIZER

Active ingredient[s]

Alcohol 80% v/v

Purpose

Antiseptic

Use[s]

Health care personnel hand rub to help reduce bacteria that potentially can cause disease.

Warnings

For external use only. Flammable. Keep away from heat or Flame

Do not use

- On children less than 2 months of age
- On open skin wounds

When using this product keep out of eyes, ears, and mouth. In case of contact with eyes, rinse eyes thoroughly with water.

Stop use and ask a doctor if irritation or rash occurs. These may be signs of a serious condition.

Keep out of reach of children. If swallowed, get medical help or contact a Poison Control Center right away.

Directions

- Place enough product on hands to cover all surfaces. Rub hands together until dry.
- Supervise children under 6 years of age when using this product to avoid swallowing.

Other information

- Store between 15-30°C (59-86°F)
- Avoid freezing and excessive heat above 40°C (104°F)

INACTIVE INGREDIENT

Inactive ingredients: glycerin, hydrogen peroxide, methylcellulose, purified water USP

Kills 99.99% of many common germs and bacteria.

Distributed By:

Cross Country Media & Sourcing

8825 Boggy Creek Road

Orlando, FL 32824

www.ccmspack.com

MADE IN USA